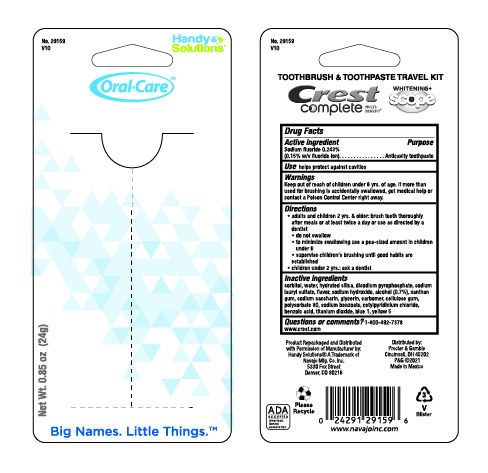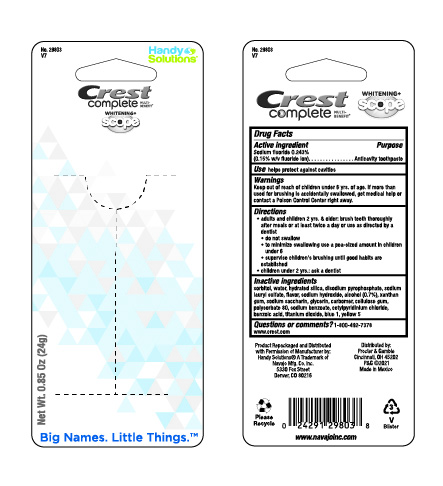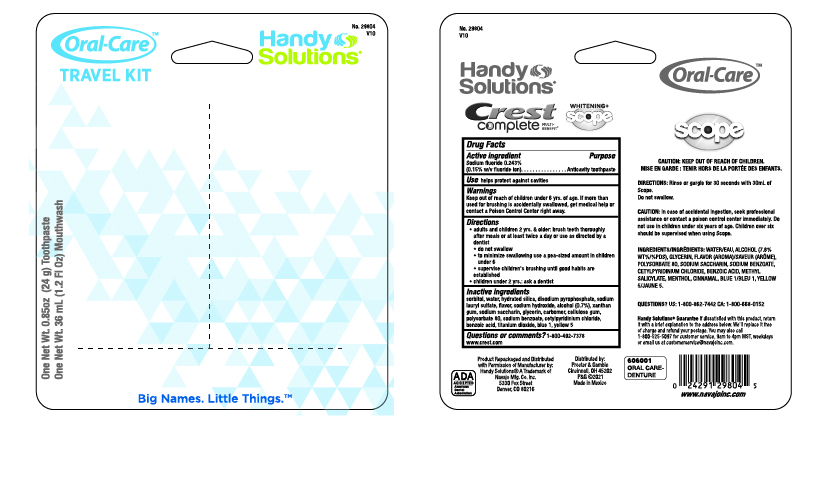 DRUG LABEL: Handy Solutions Crest Complete MULTI-BENEFIT WHITENING plus Scope
NDC: 67751-095 | Form: PASTE, DENTIFRICE
Manufacturer: Navajo Manufacturing Company Inc
Category: otc | Type: HUMAN OTC DRUG LABEL
Date: 20250429

ACTIVE INGREDIENTS: SODIUM FLUORIDE 1.5 mg/1 g
INACTIVE INGREDIENTS: WATER; HYDRATED SILICA; SODIUM ACID PYROPHOSPHATE; SODIUM LAURYL SULFATE; SODIUM HYDROXIDE; SORBITOL; ALCOHOL; XANTHAN GUM; SACCHARIN SODIUM; GLYCERIN; CARBOXYMETHYLCELLULOSE SODIUM; POLYSORBATE 80; SODIUM BENZOATE; CETYLPYRIDINIUM CHLORIDE; BENZOIC ACID; TITANIUM DIOXIDE; FD&C BLUE NO. 1; FD&C YELLOW NO. 5

Crest Complete MULTI-BENEFIT WHITENING plus Scope

Active ingredient

Sodium fluoride 0.243%

Purpose

Anti-Cavity toothpaste

Use

helps protect against cavities

Warnings

Keep out of reach of children under 6 yrs. of age.

If more than used for brushing is accidentally swallowed, get medical help or contact a Poison Control Center right away.

Directions

- adults and children 2 yrs. and older: brush teeth thoroughly after meals or at least twice a day or use as directed by a dentist
- do not swallow
- to minimize swallowing use a pea-sized amount in children under 6
- supervise children's brushing until good habits are established
- children under 2 years : ask a dentist

Inactive ingredients

Sorbitol, water, hydrated silica, disodium pyrophosphate, sodium lauryl sulfate, flavor, sodium hydroxide, alcohol (0.7%), xanthan gum, sodium saccharin, glycerin, carbomer, cellulose gum, polysorbate 80, sodium benzoate, cetylpyridinium chloride, benzoic acid, titanium dioxide, blue 1, yellow 5

Questions or comments?

call toll-free 1-800-492-7378

PDP

Carded Crest Complete with Scope Toothpaste

Oral Care Kit with Travel Toothbrush

3PC Oral Care Kit with Scope Mouthwash and Travel Toothbrush